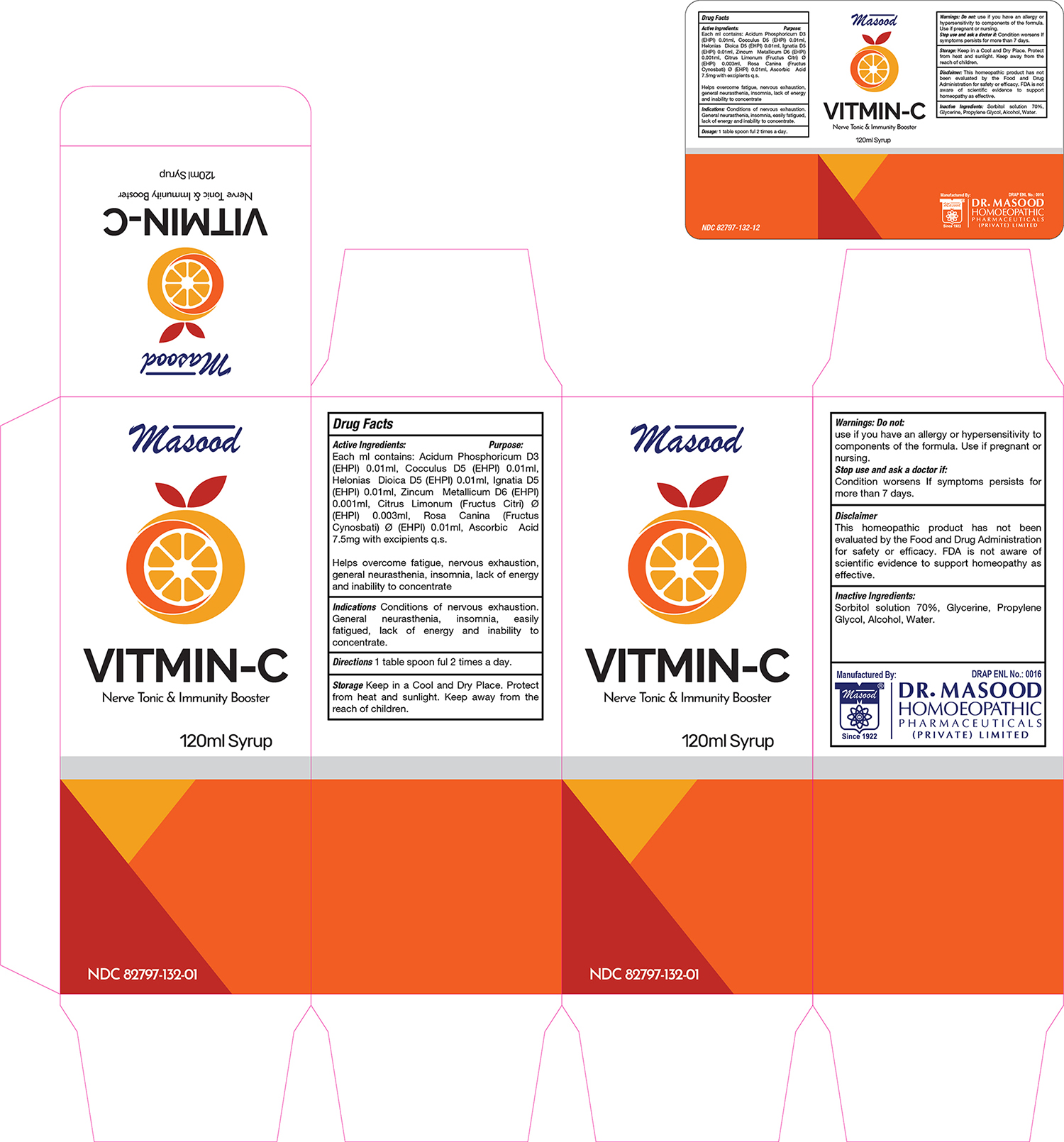 DRUG LABEL: Vitmin C
NDC: 82797-132 | Form: SYRUP
Manufacturer: Dr. Masood Homeopathic Pharmaceuticals Private Limited
Category: homeopathic | Type: HUMAN OTC DRUG LABEL
Date: 20250424

ACTIVE INGREDIENTS: ROSA CANINA WHOLE 0.01 mg/120 mL; ZINC 0.01 mg/120 mL; ASCORBIC ACID 7.5 mg/120 mL; STRYCHNOS IGNATII WHOLE 0.01 mg/120 mL; CITRUS LIMON WHOLE 0.003 mg/120 mL; CHAMAELIRIUM LUTEUM WHOLE 0.01 mg/120 mL; ANAMIRTA COCCULUS WHOLE 0.01 mg/120 mL; PHOSPHORIC ACID 0.01 mg/120 mL
INACTIVE INGREDIENTS: SORBITOL SOLUTION 70% 0.35 mL/120 mL; PROPYLENE GLYCOL DIACETATE 0.15 mL/120 mL; ALCOHOL 0.06 mL/120 mL; WATER 120 mL/120 mL; GLYCERIN 0.15 mL/120 mL

Dosage and Administration

1 tablespoonfull 2 times a day

Inactive Ingredients

Sorbitol solution 70%

Glycerine

Propylene Glycol

Alcohol

Water

Indications and Usage

Conditions of Nervous Exhaustion

General Neurasthenia

Insomnia

Fatigue

Lack of Energy

Inability to concentrate

Active Ingredients

Acid Phosphoricum

Cocculus

Helonias Diocia

Ignatia

Zincum Mettalicum

Citrus Limonum

Rosa Canina

Ascorbic Acid

Keep out of the reach of children

Keep this and all other medicines out of the reach of children

Warnings

Do not:

- use if you have an allergy or hypersensitivity to components of the formula
- use if pregnant or nursing

Stop use and ask a doctor if:

- condition worsens
- If symptoms persists for more than 7 days

Purpose

Acid Phosphoricum Helps overcome fatigue

Cocculus Helps to maintain healthy bone growth and cognitive function

Helonias Diocia Helps overcome weakness

Ignatia Helpful for mental and physical stress

Zincum Mettalicum Helps treating Anemia

Citrus Limonum Helps smooth blood circulation

Rosa Canina supporting immune health, improving skin vitality, and aids in weight management and heart health.

Ascorbic Acid Useful for performing many vital functions in the body